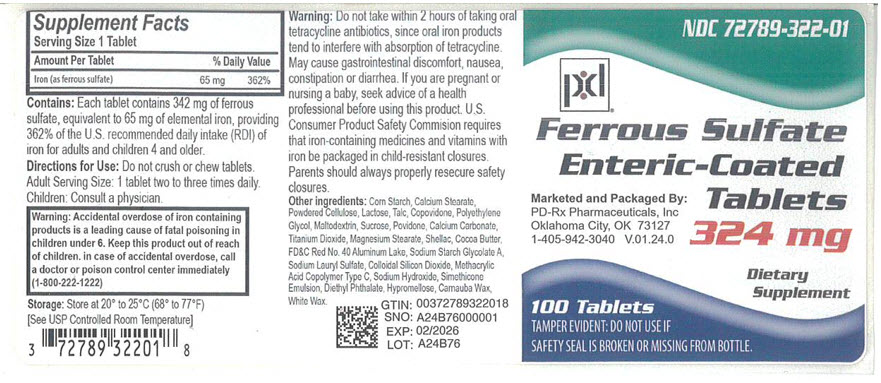 DRUG LABEL: Ferrous Sulfate
NDC: 72789-322 | Form: TABLET
Manufacturer: PD-Rx Pharmaceuticals, Inc.
Category: other | Type: DIETARY SUPPLEMENT
Date: 20251205

ACTIVE INGREDIENTS: FERROUS SULFATE 65 mg/1 1
INACTIVE INGREDIENTS: STARCH, CORN; CALCIUM STEARATE; POWDERED CELLULOSE; LACTOSE, UNSPECIFIED FORM; TALC; COPOVIDONE K25-31; POLYETHYLENE GLYCOL, UNSPECIFIED; MALTODEXTRIN; SUCROSE; POVIDONE, UNSPECIFIED; CALCIUM CARBONATE; TITANIUM DIOXIDE; MAGNESIUM STEARATE; SHELLAC; COCOA BUTTER; FD&C RED NO. 40; SODIUM LAURYL SULFATE; SILICON DIOXIDE; METHACRYLIC ACID AND ETHYL ACRYLATE COPOLYMER; SODIUM HYDROXIDE; DIETHYL PHTHALATE; HYPROMELLOSE, UNSPECIFIED; CARNAUBA WAX; WHITE WAX

FERROUS SULFATE
ENTERIC-COATED TABLETS

STATEMENT OF IDENTITY

Dietary Supplement

CONTAINS:

Each tablet contains 324 mg of ferrous sulfate, equivalent to 65 mg of elemental iron, providing 362% of the U.S. recommended daily intake (RDI) of iron for adults and children 4 and older.

DIRECTIONS FOR USE:

Do not crush or chew tablets. Adult Serving Size: 1 tablet two to three times daily. Children: Consult a physician.

WARNING:

Accidental overdose of iron-containing products is a leading cause of fatal poisoning in children under 6. Keep this product out of reach of children. In case of accidental overdose, call a doctor or poison control center immediately.

WARNINGS:

Do not take within 2 hours of taking oral tetracycline antibiotics, since oral iron products tend to interfere with absorption of tetracycline. May cause gastrointestinal discomfort, nausea, constipation or diarrhea. If you are pregnant or nursing a baby, seek advice of a health professional before using this product. U.S. Consumer Product Safety Commission requires that iron-containing medicines and vitamins with iron be packaged in child-resistant closures. Parents should always properly resecure safety closures.

STORAGE:

Store at 20° to 25°C (68° to 77°F) [see USP Controlled Room Temperature]

Supplement Facts

Serving Size 1 Tablet
Amount Per Tablet | % Daily Value
Iron (as ferrous sulfate) | 65 mg | 362%

Other ingredients: Corn Starch, Calcium Stearate, Powdered Cellulose, Lactose, Talc, Copovidone, Polyethylene Glycol, Maltodextrin, Sucrose, Povidone, Calcium Carbonate, Titanium Dioxide, Magnesium Stearate, Shellac, Cocoa Butter, FD&C Red No. 40 Aluminum Lake, Sodium Starch Glycolate A, Sodium Lauryl Sulfate, Colloidal Silicon Dioxide, Methacrylic Acid Copolymer Type C, Sodium Hydroxide, Simethicone Emulsion, Diethyl Phthalate, Hypromellose, Carnauba Wax, White Wax.

Packaged by: Paddock Laboratories, Inc.
Minneapolis, MN 55427

(01-08)

16 HOW SUPPLIED

Ferrous Sulfate Tablets are available as follows:

Each tablet contains 324mg of ferrous sulfate, equivalent to 65mg of elemental iron, providing 362% of the U.S. recommended daily intake (RDI) of iron for adults and children 4 and older.

Available in bottles of 100 tablets (NDC 72789-322-01)

PRINCIPAL DISPLAY PANEL - 324 mg Tablet Bottle Label

NDC 72789-322-01

Ferrous Sulfate
Enteric-Coated
Tablets

324 mg

Dietary
Supplement

Marketed and Packaged By:
PD-Rx Pharmaceuticals, Inc
Oklahoma City, OK 73127
1-405-942-3040 V.01.24.0

100 Tablets
TAMPER EVIDENT: DO NOT USE IF
SAFETY SEAL IS BROKEN OR MISSING FROM BOTTLE.